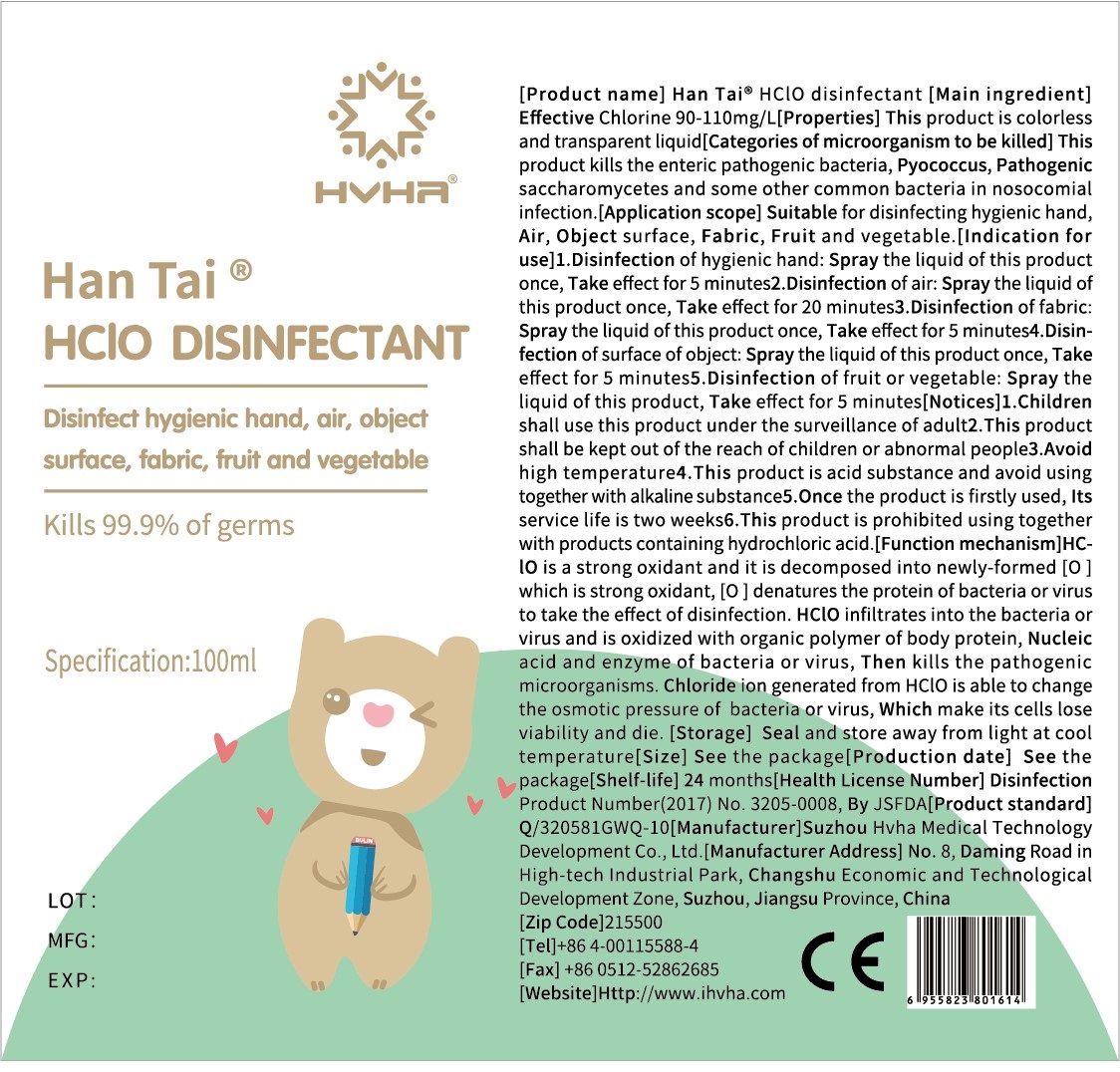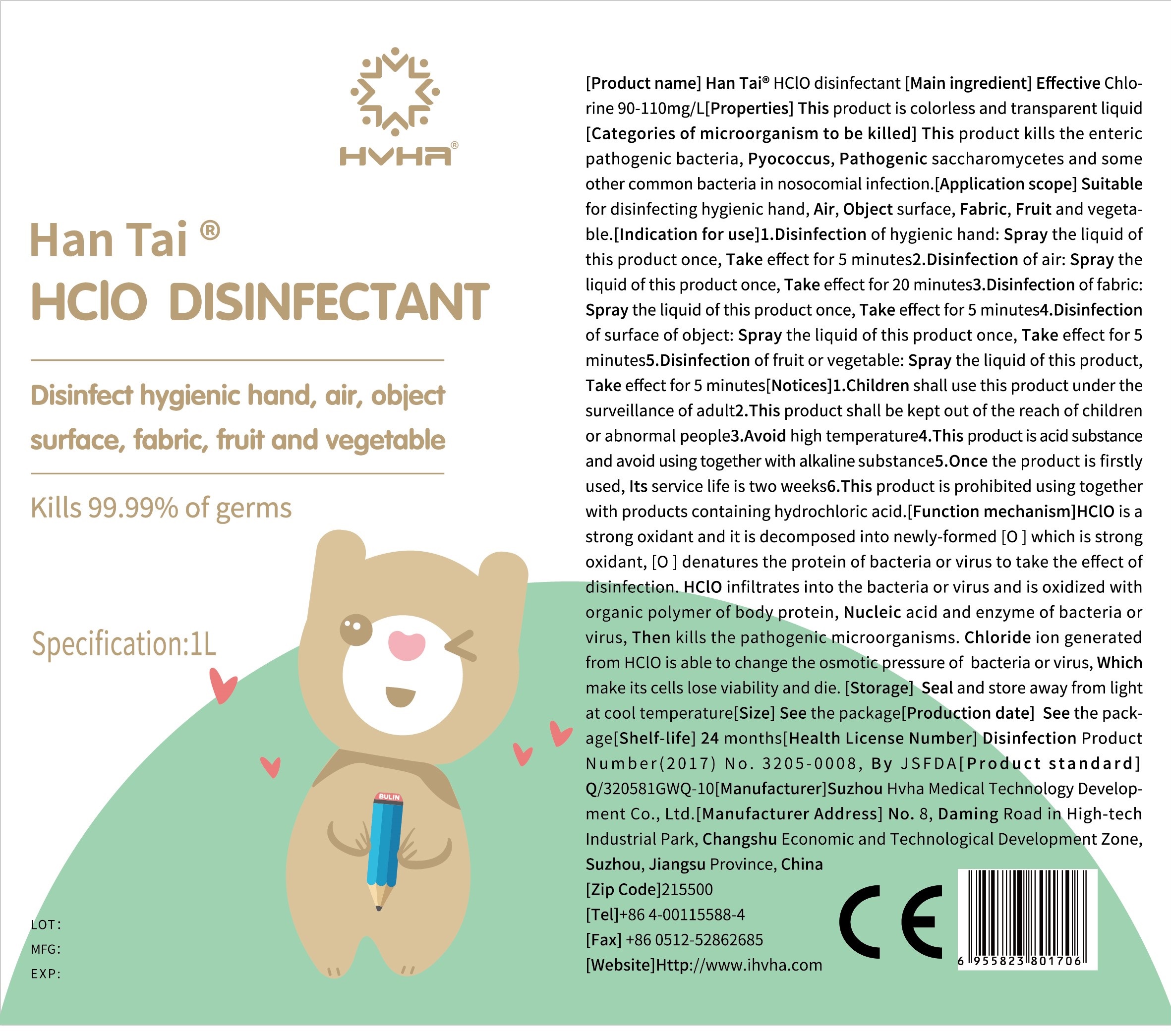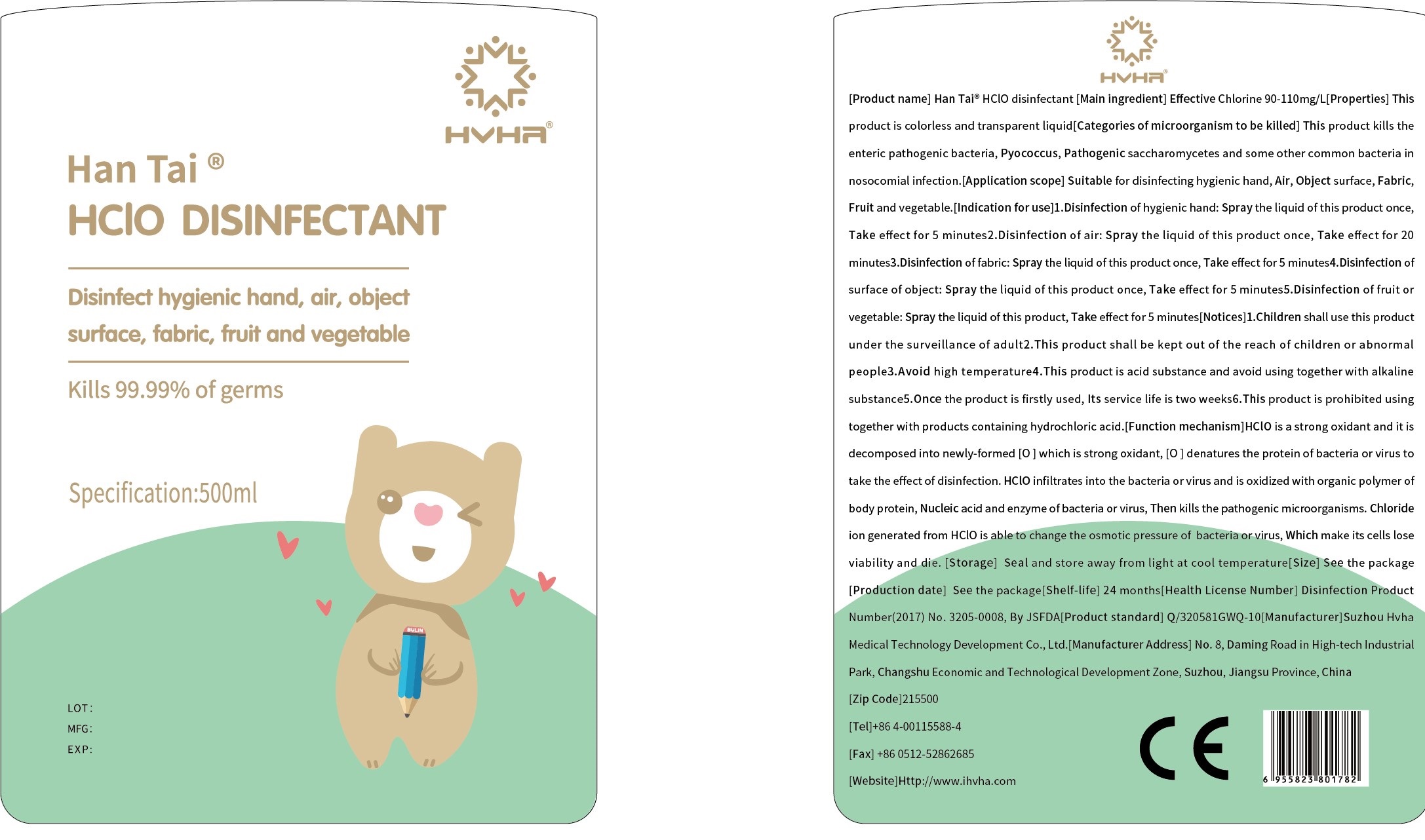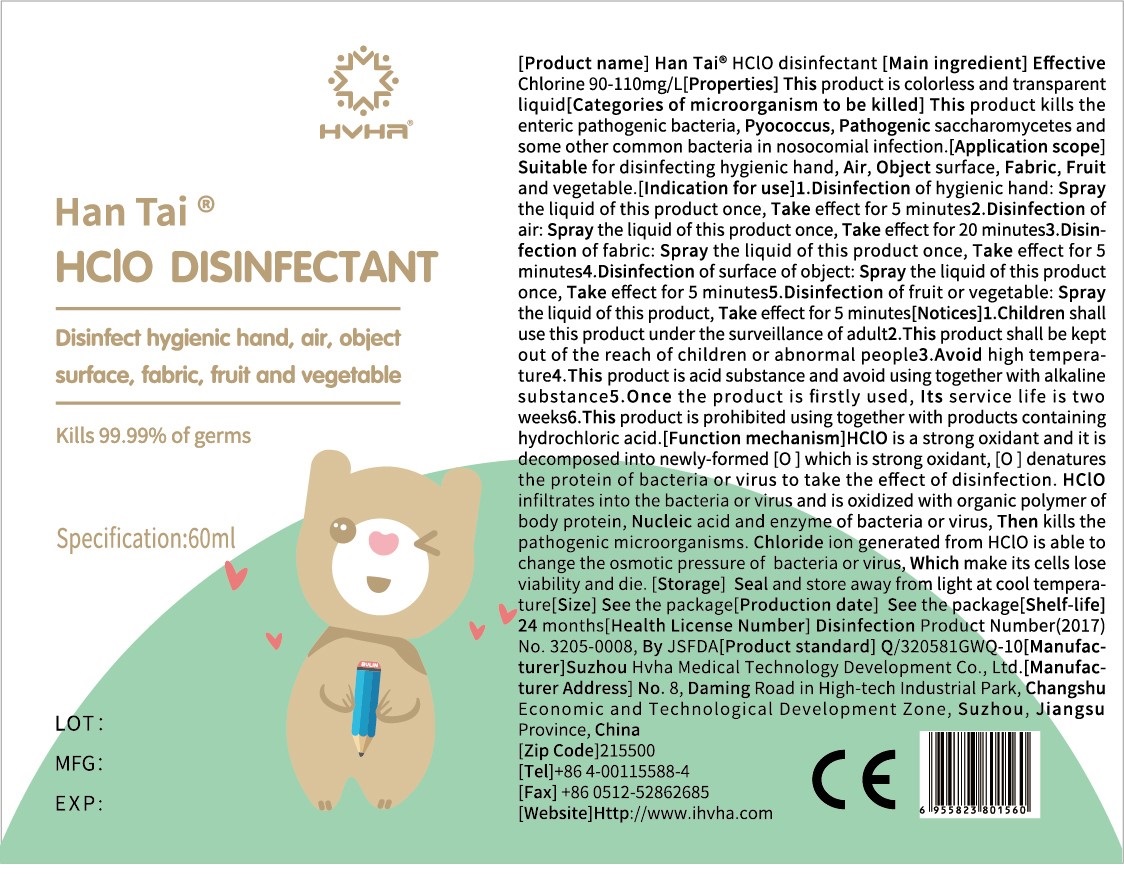 DRUG LABEL: HClO disinfectant
NDC: 77263-001 | Form: LIQUID
Manufacturer: Suzhou HVHA Medical Technology Development Co.,Ltd.
Category: otc | Type: HUMAN OTC DRUG LABEL
Date: 20211228

ACTIVE INGREDIENTS: HYPOCHLOROUS ACID 0.1 mg/1 mL
INACTIVE INGREDIENTS: WATER; SODIUM CHLORIDE; SODIUM SILICATE

Han Tai® HClO disinfectant

Main ingredient

Effective Chlorine 90-110mg/L

Properties

This product is colorless transparent liquid

Categories of microorganism to be killed

This product kills the enteric pathogenic bacteria, pyococcus, pathogenic saccharomycetes and common bacteria in nosocomial infection.

Application scope

Suitable for disinfecting hygienic hand, Air, Object surface, Fabric, Fruit and vegetable

Indication for use

1. Disinfection of hand: Spray the original solution once, take effect for 5 minutes.

2. Disinfection of air: Spray the original solution once, take effect for 20 minutes.

3. Disinfection of fabric: Spray the original solution once, take effect for 5 minutes.

4. Disinfection of surface of object: Spray the original solution once, take effect for 5 minutes.

5. Disinfection of fruit or vegetable: Spray the original solution, take effect for 5 minutes.

Notices

Use by children must be under tutelage of adult.

Keep out of reach of children and abnormal people.

WARNINGS

Avoid high temperature or open fire

This product is acid substance and avoid using together with alkaline substance.

After the product is opened, the service life is two weeks.

This product is prohibited using together with products containing hydrochloric acid.

Function mechanism

HCLO is a kind of strong oxidant and it is decomposed into nascent oxygen which is strong oxidability to makes proteins and other substances of bacteria or virus denatured and play a bactericidal effect. HCLO infiltrates into the bacteria or virus and oxidizes with organic macromolecules such as protein, nucleic acid and enzyme, and enzymes to kill the pathogenic microorganisms. The chloride ion generated from HCLO can also significantly change the osmotic pressure of bacteria or virus, making their cells lose viability and die.

Storage

Seal and store away from light at cool temperature

Shelf life: 24 months

Inactive ingredients

Water, Sodium chloride, Sodium silicate

Purpose

Disinfect hand, air, surface of object, fabric, fruit and vegetable